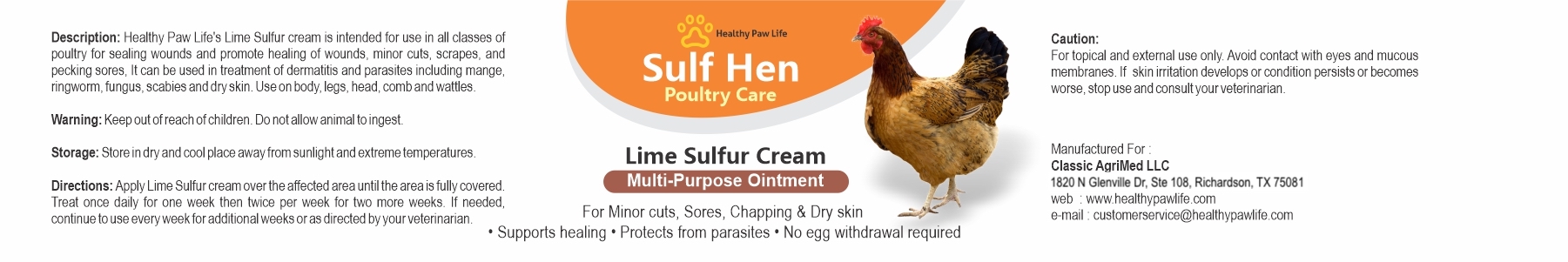 DRUG LABEL: SULF HEN LIME SULFUR
NDC: 86130-501 | Form: CREAM
Manufacturer: CLASSIC AGRIMED LLC
Category: animal | Type: OTC ANIMAL DRUG LABEL
Date: 20231118

ACTIVE INGREDIENTS: CALCIUM POLYSULFIDE 0.16 g/100 g

SULF HEN LIME SULFUR

Healthy Paw Life's Lime Sulfur cream is intended for use in all classes of polutry for sealing wounds and promite heaing of wounds, minor cuts, scrapes and pecking sores. It can be used in treatment of dermatitis and parasites including mange, ringworm, fungus, scabies and dry skin. Use on body, legs, head, comb and wattles

WARNING:
Keep out of reach of children. Do not allow animal to ingest

STORAGE:
Store in dry and cool place away from sunlight and extreme temperatures

DIRECTIONS:
Apply Lime Sulfur cream over the affected area until the area is fully covered. Treat once daily for one week then twice per week for two more weeks. If needed continue to use every week for additional weeks or as directed by the veterinarian.

CAUTION:
For topical and external use only. Avoid contact with eyes and mucous membranes. If skin irritation develops or condition persists or becomes worse, stop use and consult your veterinarian.